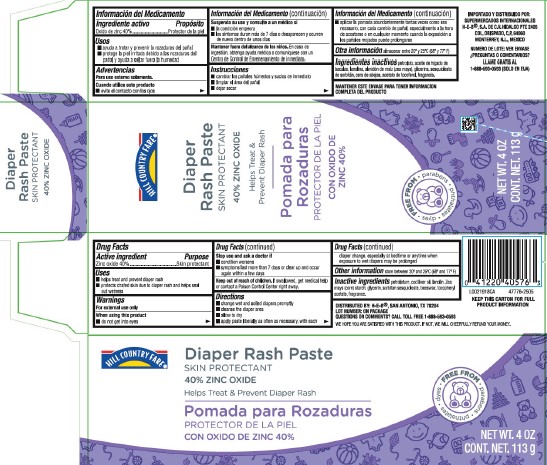 DRUG LABEL: Diaper Rash
NDC: 37808-020 | Form: PASTE
Manufacturer: H E B
Category: otc | Type: HUMAN OTC DRUG LABEL
Date: 20260224

ACTIVE INGREDIENTS: ZINC OXIDE 400 mg/1 g
INACTIVE INGREDIENTS: PETROLATUM; COD LIVER OIL; LANOLIN; STARCH, CORN; GLYCERIN; SORBITAN SESQUIOLEATE; YELLOW WAX; .ALPHA.-TOCOPHEROL ACETATE

HEB Hill Country 020.002/020AC-AD
Diaper Rash Ointment 40% Zinc Oxide

Active ingredient

Zinc oxide 40%

Purpose

Skin protectant

Uses

- helps treat and prevent diaper rash
- protects chafed skin due to diaper rash and helps seal out wetness

Warnings

For external use only

When using this product

- do not get into eyes

Stop use and ask a doctor if

- condition worsens
- symptoms last more than 7 days or clear up and occur again within a few days

Keep out of reach of children.

If swallowed, get medical help or contact a Poison Control Center right away.

Directions

- change wet and soilded diapers promptly
- cleanse the diaper area
- allow to dry
- apply paste liberally as often as necessary, with each diaper change, especially at bedtime or anytime when exposure to wet diapers may be prolonged

Other information

store between 20⁰ and 25⁰C (68⁰ and 77⁰F)

Inactive ingredients

petrolatum, cod liver oil, lanolin, Zea mays (corn) starch, glycerin, sorbitan sesquioleate, beeswax, tocopheryl acetate, fragrance

Adverse Reactions

KEEP THIS CARTON FOR FULL PRODUCT INFORMATION

DISTRIBUTED BY: H-E-B®, SAN ANTONIO, TN 78204

LOT NUMBER: ON PACKAGE

QUESTIONS OR COMMENTS? CALL TOLL FREE 1-888-593-0593

WE HOPE YOU ARE SATISFIED WITH THIS PRODUCT. IF NOT, WE WILL CHEERFULLY REFUND YOUR MONEY.

Principal display panel

HILL COUNTRY FARE®

Diaper Rash Paste

SKIN PROTECTANT

40% ZINC OXIDE

Helps Soothe & Prevent Diaper Rash

FREE FROM

- parabens
- phthalates
- dyes

NET WT. 4 OZ

CONT. NET. 113 g